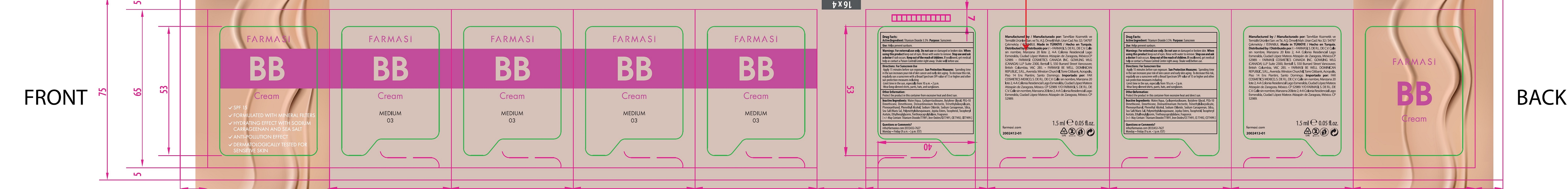 DRUG LABEL: Farmasi BB Cream- MEDIUM 03
NDC: 78317-054 | Form: CREAM
Manufacturer: TAN ALIZE KOZMETIK VE TEMIZLIK URUNLERI SANAYI VE TICARET ANONIM SIRKETI
Category: otc | Type: HUMAN OTC DRUG LABEL
Date: 20231023

ACTIVE INGREDIENTS: TITANIUM DIOXIDE 35 mg/1 mL
INACTIVE INGREDIENTS: WATER; CYCLOMETHICONE 5; BUTYLENE GLYCOL; DIMETHICONE; DISTEARDIMONIUM HECTORITE; PHENOXYETHANOL; PHENYLETHYL ALCOHOL; SODIUM CHLORIDE; CARRAGEENAN SODIUM; SILICON DIOXIDE; SEA SALT; POLYMETHYLSILSESQUIOXANE (4.5 MICRONS); TOCOPHEROL; .ALPHA.-TOCOPHEROL ACETATE; ETHYLHEXYLGLYCERIN; TRIETHOXYCAPRYLYLSILANE; FERRIC OXIDE RED; FERRIC OXIDE YELLOW; FERROSOFERRIC OXIDE

Farmasi BB Cream- MEDIUM 03

Active Ingredient:

Titanium Dioxide 3.5%

Purpose:

Sunscreen

Use:

Helps prevent sunburn.

Warnings:

For external use only.

Do not use

on damaged or broken skin.

When using this product

keep out of eyes. Rinse with water to remove.

Stop use and ask a doctor if

rash occurs.

Keep out of reach of the children.

If swallowed, get medical help or contact a Poison Control Center right away. Shake well before use.

Directions: For Sunscreen Use

- Apply 15 minutes before sun exposure. Sun Protection Measures:Spending time in the sun increases your risk of skin cancer and early skin aging. To decrease this risk, regularly use a sunscreen with a Broad Spectrum SPF value of 15 or higher and other sun protection measures including
- Limit time in the sun, especially from 10 a.m. – 2 p.m.
- Wear long-sleeved shirts, pants, hats, and sunglasses.

Other Information:

Protect the product in this container from excessive heat and direct sun.

Inactive Ingredients:

Water/Aqua, Cyclopentasiloxane, Butylene Glycol, PEG-10 Dimethicone, Dimethicone, Disteardimonium Hectorite, Trimethylsiloxysilicate, Phenoxyethanol, Phenethyl Alcohol, Sodium Chloride, Sodium Carrageenan, Silica, Sea Salt/Maris Sal, Polymethylsilsesquioxane, Jojoba Esters, Tocopherol, Tocopheryl Acetate, Ethylhexylglycerin, Triethoxycaprylylsilane, Fragrance.(+/- May Contain: Titanium Dioxide/CI77891, Iron Oxides/CI 77491,CI 77492, CI77499.)

Questions or Comments?

info@farmasius.com (833) 432-7627

Monday - Friday (9 a.m -) p.m. EST)